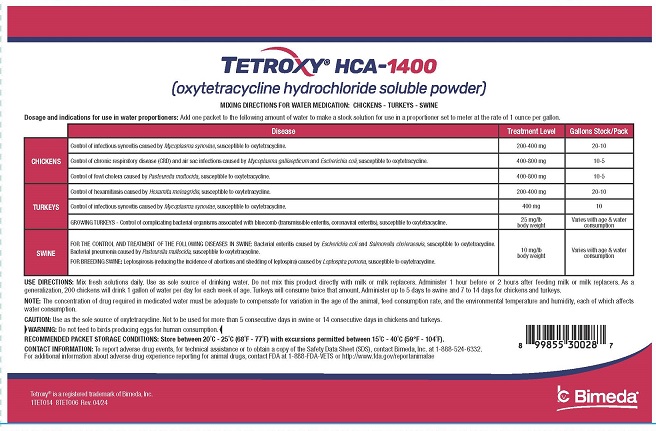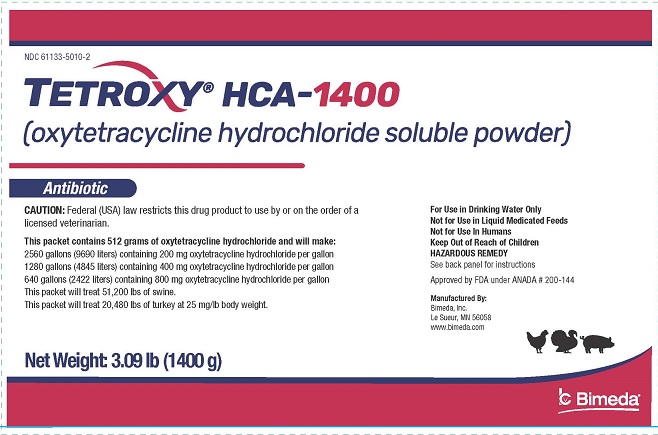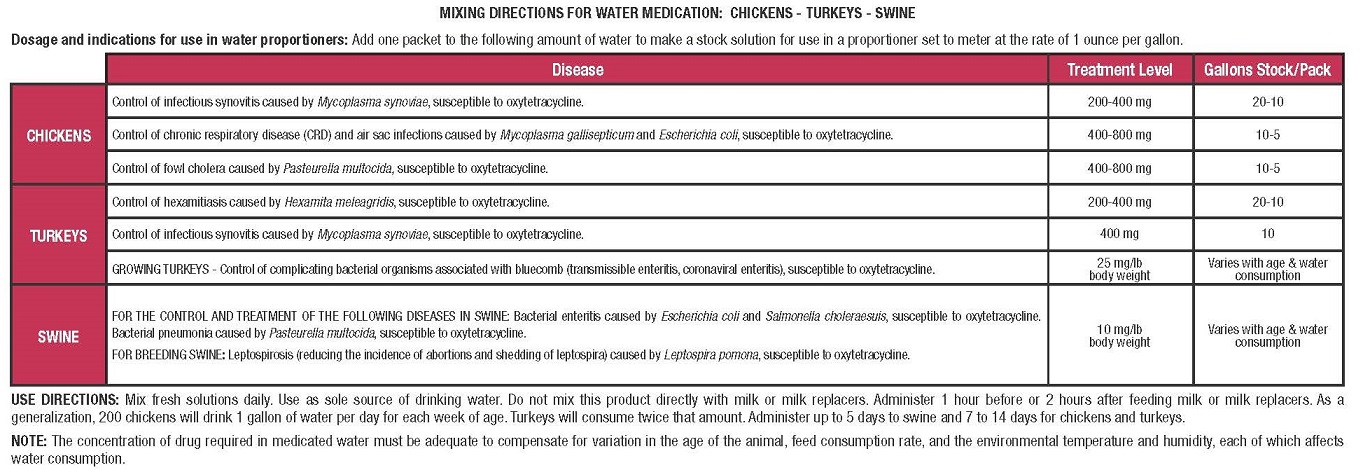 DRUG LABEL: Tetroxy HCA
NDC: 61133-5010 | Form: POWDER
Manufacturer: Bimeda, Inc.
Category: animal | Type: PRESCRIPTION ANIMAL DRUG LABEL
Date: 20241211

ACTIVE INGREDIENTS: OXYTETRACYCLINE HYDROCHLORIDE 648 g/1772 g

DESCRIPTION

Tetroxy® HCA-1400
(oxytetracycline hydrochloride soluble powder)
Antibiotic
CAUTION: Federal (USA) law restricts this drug to use by or on the order of a licensed veterinarian.

This packet contains 512 g of oxytetracycline hydrochloride and will make:
2560 gallons (9690 liters) containing 200 mg oxytetracycline hydrochloride per gallon
1280 gallons (4845 liters) containing 400 mg oxytetracycline hydrochloride per gallon
640 gallons (2422 liters) containing 800 mg oxytetracycline hydrochloride per gallon
This packet will treat 51,200 lbs of swine.
This packet will treat 20,480 lbs of turkey at 25 mg/lb body weight.

For Use in Drinking Water Only
Not For Use in Liquid Medicated Feeds
Not For Use in Humans
Keep Out of Reach of Children
HAZARDOUS REMEDY
See back panel for instructions.
Approved by FDA under ANADA # 200-144

Net Weight: 3.09 lb (1400 g)

PRECAUTIONS

CAUTION: Use as the sole source of oxytetracycline. Not to be used for more than 5 consecutive days in swine or 14 consecutive days in chickens and turkeys.

RESIDUE WARNING

WARNING: Do not feed to birds producing eggs for human consumption.

STORAGE AND HANDLING

RECOMMENDED PACKET STORAGE CONDITIONS: Store between 20°C - 25°C (68°F - 77°F) with excursions permitted between 15°C - 40°C (59°F - 104°F).

CONTACT INFORMATION: To report adverse events, for technical assistance or to obtain a copy of the Safety Data Sheet (SDS), contact Bimeda, Inc. at 1-888-524-6332. For additional information about adverse drug experience reporting for animal drugs, contact FDA at 1-888-FDA-VETS or http://www.fda.gov/reportanimalae